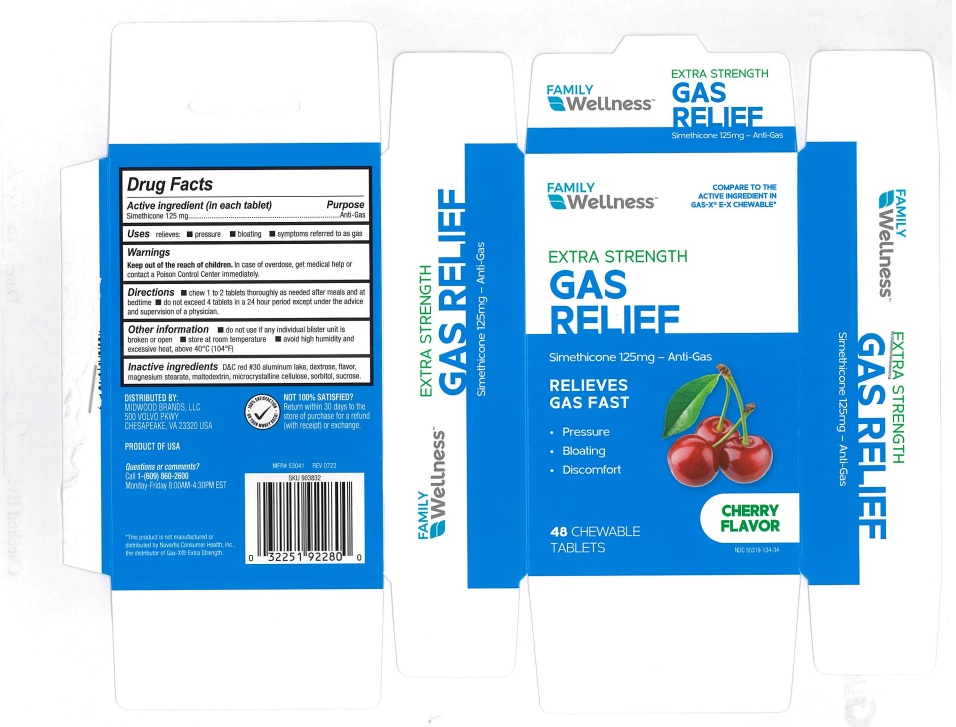 DRUG LABEL: Family Wellness Extra Strength Gas Relief Cherry
NDC: 55319-134 | Form: TABLET, CHEWABLE
Manufacturer: Family Dollar Services, Inc.
Category: otc | Type: Human OTC Drug Label
Date: 20240223

ACTIVE INGREDIENTS: DIMETHICONE 125 mg/1 1
INACTIVE INGREDIENTS: D&C RED NO. 30; MAGNESIUM STEARATE; CELLULOSE, MICROCRYSTALLINE; SORBITOL; SUCROSE; MALTODEXTRIN; DEXTROSE, UNSPECIFIED FORM

Family Wellness Extra Strength Gas Relief Cherry - 134

ACTIVE INGREDIENT(in each tablet)

Simethicone 125 mg

PURPOSE

Anti-gas

USE(S)

relieves:

- pressure
- bloating
- symptoms referred to as gas

WARNINGS

.

KEEP OUT OF REACH OF CHILDREN

In case of overdose, get medical help or contact a poison control center immediately.

DIRECTIONS

- chew 1 to 2 tablets thoroughly as needed after meals and at bedtime
- do not exceed 4 tablets in a 24 hour period except under the advice and supervision of a physician.

OTHER INFORMATION

- do not use if any individual blister unit is broken or open
- store at room temperature
- avoid high humidity and excessive heat, above 40ºC (104ºF)

INACTIVE INGREDIENTS

D&C red # 30 aluminum lake, dextrose, flavor, magnesium stearate, maltodextrin, microcrystalline cellulose, sorbitol, sucrose.

PRINCIPAL DISPLAY PANEL

Family WellnessTM

COMPARE TO THE ACTIVE INGREDIENT IN GAS-X® E-X CHEWABLE*

EXTRA STRENGTH

GAS RELIEF

Simethicone 125 mg - Anti-Gas

RELIEVES GAS FAST

Pressure

Bloating

Gas Distress

48 CHEWABLE TABLETS

CHERRY FLAVOR

NDC 55319-134-34